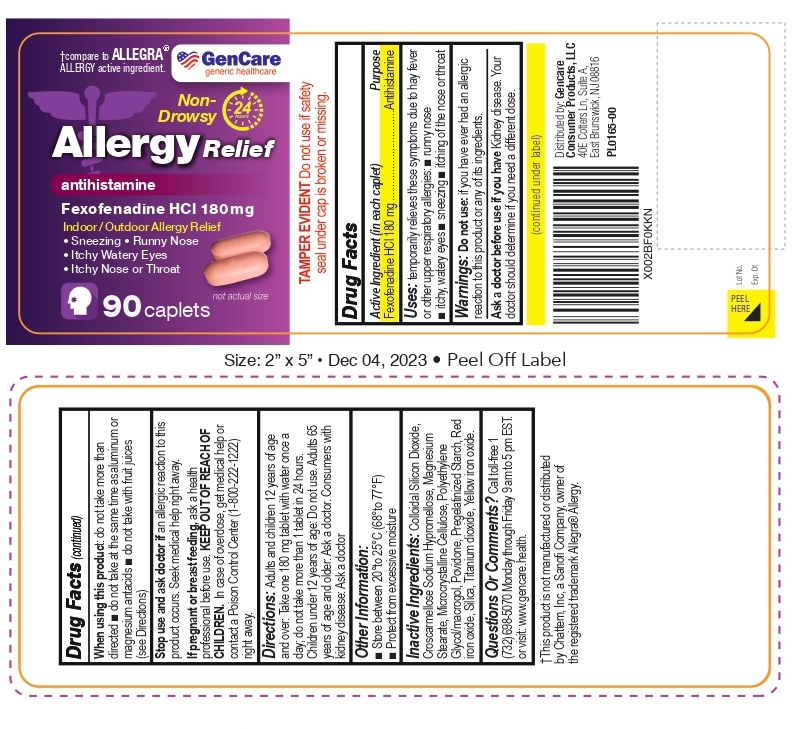 DRUG LABEL: FEXOFENADINE HYDROCHLORIDE
NDC: 72090-010 | Form: TABLET
Manufacturer: Pioneer Life Sciences, LLC
Category: otc | Type: HUMAN OTC DRUG LABEL
Date: 20251226

ACTIVE INGREDIENTS: FEXOFENADINE HYDROCHLORIDE 180 mg/1 1
INACTIVE INGREDIENTS: FERRIC OXIDE YELLOW; SILICON DIOXIDE; CROSCARMELLOSE SODIUM; HYPROMELLOSE, UNSPECIFIED; MAGNESIUM STEARATE; MICROCRYSTALLINE CELLULOSE; POLYETHYLENE GLYCOL, UNSPECIFIED; POVIDONE; STARCH, CORN; FERRIC OXIDE RED; TITANIUM DIOXIDE

Allergy Relief Fexofenadine Hydrochlroride Tablets 180 mg

Active ingredient (in each caplet)

Fexofenadine HCl 180 mg

Purpose

Antihistamine

Uses

temporarily relieves these symptoms due to hay fever or other upper respiratory allergies:
 runny nose  sneezing  itchy, watery eyes  itching of the nose or throat

Do not use if you have ever had an allergic reaction to this product or any of its ingredients.

Ask a doctor before use if you have kidney disease. Your doctor should determine if you need a different dose.

When using this product  do not take more than directed  do not take at
the same time as aluminum or magnesium antacids  do not take with fruit juices (see Directions)

Stop use and ask a doctor if an allergic reaction to this product occurs. Seek medical help right away.

PREGNANCY OR BREAST FEEDING

If pregnant or breast-feeding, ask a health professional before use.

Keep out of reach of children. In case of overdose, get medical help or contact a Poison Control Center (1-800-222-1222) right away.

Directions

adults and children 12 years of age and over | take one 180 mg tablet with water once a day; do not take more than 1 tablet in 24 hours
children under 12 years of age | do not use
adults 65 years of age and older | ask a doctor
consumers with kidney disease | ask a doctor

Other information  store between 20º and 25ºC (68º and 77ºF)  protect from excessive moisture

INACTIVE INGREDIENT

Inactive ingredients: colloidal silicone dioxide, croscarmellose sodium, hypromellose, magnesium stearate, microcrystalline cellulose, polyethylene glycol/macrogol, povidone, pregelatinized starch, red iron oxide, silica, titanium dioxide, yellow iron oxide.

Questions or comments? Call toll-free 1 (732) 698-5070 Monday through Friday 9 am to 5 pm EST.
or visit: www.gencare.health.

Distributed by: Gencare Consumer Products, LLC
40E Cotters Ln, Suite A,
East Brunswick, NJ 08816